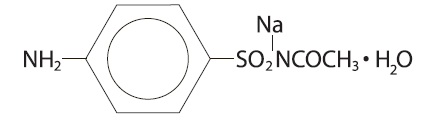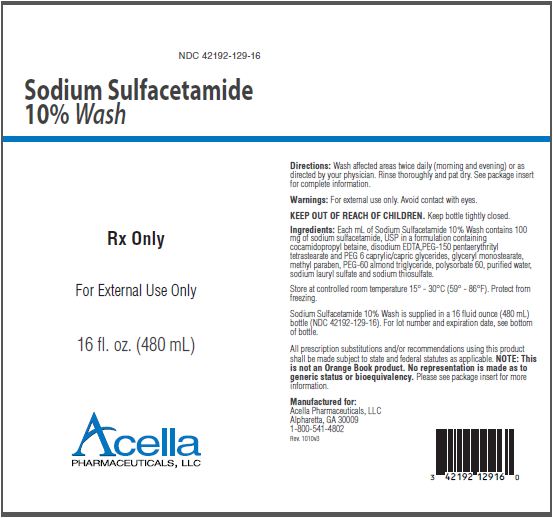 DRUG LABEL: SODIUM SULFACETAMIDE
NDC: 42192-129 | Form: LIQUID
Manufacturer: Acella Pharmaceuticals, LLC
Category: prescription | Type: HUMAN PRESCRIPTION DRUG LABEL
Date: 20240111

ACTIVE INGREDIENTS: SULFACETAMIDE SODIUM 100 mg/1 mL
INACTIVE INGREDIENTS: COCAMIDOPROPYL BETAINE; EDETATE DISODIUM; PENTAERYTHRITYL TETRASTEARATE; CAPRYLIC/CAPRIC MONO/DIGLYCERIDES; GLYCERYL MONOSTEARATE; METHYLPARABEN; PEG-60 ALMOND GLYCERIDES; POLYSORBATE 60; WATER; SODIUM LAURETH SULFATE; SODIUM THIOSULFATE

Sodium Sulfacetamide 10% Wash
Rx Only

DESCRIPTION:

Sodium sulfacetamide is C8H9N2NaO3S·H2O with molecular weight of 254.24. Chemically, it is Acetamide N-[(4-aminophenyl) sulfonyl]-acetamide, monosodium salt, monohydrate. The structural formula is:

Each gram of Sodium Sulfacetamide 10% Wash contains 100 mg of Sodium Sulfacetamide, USP in a formulation containing cocamidopropyl betaine, disodium EDTA,PEG-150 pentaerythrityl tetrastearate and PEG 6 caprylic/capric glycerides, glyceryl monostearate, methyl paraben, PEG-60 almond triglyceride, polysorbate 60, purified water, sodium lauryl sulfate and sodium thiosulfate.

Sodium Sulfacetamide is an odorless, white, crystalline powder with a bitter taste. It is freely soluble in water, sparingly soluble in alcohol, while practically insoluble in benzene, in chloroform and in ether.

CLINICAL PHARMACOLOGY:

Sodium sulfacetamide exerts a bacteriostatic effect against sulfonamide sensitive Gram-positive and Gram-negative microorganisms commonly isolated from secondary cutaneous pyogenic infections. It acts by restricting the synthesis of folic acid required by bacteria for growth, by its competition with para-aminobenzoic acid. There is no clinical data available on the degree and rate of systemic absorption of Sodium Sulfacetamide 10% Wash when applied to the skin or scalp. However, significant absorption of sodium sulfacetamide through the skin has been reported.

The following in vitro data is available but the clinical significance is not known. Organisms which show susceptibility to sodium sulfacetamide are: Streptococci, Staphylococci, E. coli, Klebsiella pneumonia, Pseudomonas pyocyanea, Salmonella species, Proteus vulgaris, Nocardia and Actinomyces .

INDICATIONS:

Sodium Sulfacetamide 10% Wash is intended for topical application in the following scaling dermatoses: seborrheic dermatitis and seborrhea sicca (dandruff). It is also indicated for the treatment of secondary bacterial infections of the skin due to organisms susceptible to sulfonamides.

CONTRAINDICATIONS:

Sodium Sulfacetamide 10% Wash is contraindicated for use by patients having known hypersensitivity to sulfonamides or any other component of this product.

WARNINGS:

Sulfonamides are known to cause Stevens-Johnson syndrome in hypersensitivie individuals. Stevens-Johnson syndrome also has been reported following the use of sodium sulfacetamide topically. Cases of drug induced systemic lupus erythematosus from topical sulfacetamide also have been reported. In one of these cases, there was a fatal outcome. KEEP OUT OF THE REACH OF CHILDREN.

PRECAUTIONS:

For external use only.

GENERAL PRECAUTIONS

General - Nonsusceptible organisms, including fungi, may proliferate with the use of this preparation. Hypersensitivity reactions may recur when a sulfonamide is readministered, irrespective of the route of administration, and cross hypersensitivity between different sulfonamides may occur. If Sodium Sulfacetamide 10% Wash produces signs of hypersensitivity or other untoward reactions, discontinue use of the preparation. Systemic absorption of topical sulfonamides is greater following application to large, infected, abraded, denuded, or severely burned areas. Under these circumstances, potentially any of the adverse effects produced by the systemic administration of these agents could occur and appropriate observations and laboratory determinations should be performed.

PATIENT COUNSELING INFORMATION

Information for patients - Patients should discontinue use of Sodium Sulfacetamide 10% Wash if the condition worsens, or is a rash develops in the area being treated or elsewhere. Sodium Sulfacetamide 10% Wash also should be discontinued promptly and the physician notified if any arthritis, fever or sores in the mouth develop.

Drug Interactions:

Sodium Sulfacetamide 10% Wash is incompatible with silver preparations.

CARCINOGENESIS AND MUTAGENESIS AND IMPAIRMENT OF FERTILITY

Carcinogenesis, Mutagenesis and Impairment of Fertility - Long-term studies in animals have not been performed to evaluate carcinogenic potential. Studies on reproduction and fertility also have not been performed. Chromosomal nondisjunction in the yeast, Saccharomyces cerevisiae, following application of sodium sulfacetamide has been reported. The significance of this finding to the topical use of sodium sulfacetamide in the human is not known.

PREGNANCY:

Category C. Animal reproduction studies have not been conducted with Sodium Sulfacetamide 10% Wash. It is not known whether Sodium Sulfacetamide 10% Wash can cause fetal harm when administered to a pregnant woman or can affect reproduction capacity. Sodium Sulfacetamide 10% Wash should be given to a pregnant woman only if clearly needed or when potential benefits outweigh potential hazards to the fetus.

NURSING MOTHERS:

It is not known whether this drug is excreted in human milk. Because many drugs are excreted in human milk, caution should be when Sodium Sulfacetamide 10% Wash is administered to a nursing woman.

PEDIATRIC USE:

Safety and effectiveness in children under the age of 12 have not been established.

ADVERSE REACTIONS:

Reports of irritation and hypersensitivity to sodium sulfacetamide are uncommon. The following adverse reactions, reported after administration of sterile ophthalmic sodium sulfacetamide, are noteworthy: instances of Stevens-Johnson syndrome and instances of local hypersensitivity which progressed to a syndrome resembling systemic lupus erythematosus; in one case a fatal outcome was reported. (See warnings.)

OVERDOSAGE:

The oral LD50 of sulfacetamide in mice is 16.5 g/kg. In the event of overdosage, emergency treatment should be started immediately. Manifestations: Overdosage may cause nausea and vomiting. Large oral overdosage may cause hematuria, crystalluria and renal shutdown due to the precipitation of sulfa crystals in the renal tubules and the urinary tract. For treatment, contact your local Poison Control Center.

DOSAGE AND ADMINISTRATION:

Seborrheic dermatitis including seborrhea sicca - Wash affected areas twice daily (morning and evening), or as directed by your physician. Avoid contact with eyes or mucous membranes. Wet skin and liberally apply to areas to be cleansed, massage gently into skin working into a full lather, rinse thoroughly and pat dry. Rinsing with plain water will remove any excess medication. Repeat application as described for eight to ten days. If skin dryness occurs it may be controlled by rinsing cleanser off sooner or using less frequently. Regular shampooing following Sodium Sulfacetamide 10% Wash is not necessary, but the hair should be shampooed at least once a week. As the condition subsides, the interval between applications may be lengthened. Applications once or twice weekly or every other week may prevent recurrence. Should the condition recur after stopping therapy, the application of Sodium Sulfacetamide 10% Wash should be reinstated as at the beginning of treatment.

Secondary Cutaneuos Bacterial Infections - Wet skin and liberally apply to areas to be cleansed, massage gently into skin working into a full lather, rinse thoroughly and pat dry. Rinsing with plain water will remove any excess medication. Repeat application as described for eight to ten days. if skin dryness occurs it may be controlled by rinsing cleanser off sooner or using less often.

HOW SUPPLIED:

Sodium Sulfacetamide 10% Wash is available in 16 fluid ounce bottles, NDC 42192-129-16.

STORAGE AND HANDLING

Store at controlled room temperature, 15° - 30°C (59° - 86°F). Do not freeze.

Note: Store upright. Protect from freezing and excessive heat. The wash may tend to darken slightly on storage. Slight discoloration does not impair the efficacy or safety of the product. Occasionally, a slight yellowish discoloration may occur when an excessive amount of the wash is used and comes in contact with white fabrics. This discoloration, however, presents no problem, as it is readily removed by ordinary laundering without bleaches.

All prescription substitutions using this product shall be made subject to state and federal statutes as applicable. NOTE: this is not an Orange Book product and has not been subjected to FDA therapeutic equivalency or other equivalency testing. No representation is made as to generic status or bioequivalency. Each person recommending a prescription substitution using this product shall make such recommendations based on each such person’s professional opinion and knowledge, upon evaluating the active ingredients, excipients, inactive ingredients and chemical formulation information provided herein.

MANUFACTURED FOR: Acella Pharmaceuticals, LLC
Alpharetta, GA 30009
1-800-541-4802
Rev. 1010v2

PACKAGE LABEL - 10% Wash

NDC 42192-129-16

Sodium Sulfacetamide
10% Wash

Rx Only

For External Use Only

16 fl. oz. (480 mL)

Acella
PHARMACEUTICALS, LLC